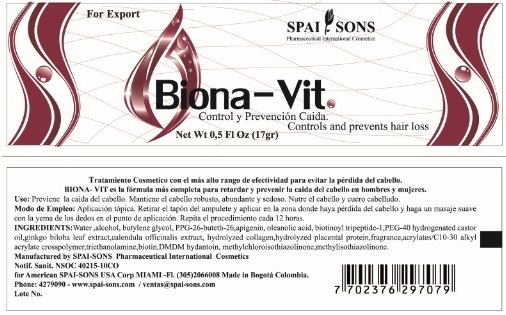 DRUG LABEL: BIONA-VIT
NDC: 66854-010 | Form: LIQUID
Manufacturer: SPAI-SONS PHARMACEUTICAL INTERNATIONAL COSMETICS
Category: otc | Type: HUMAN OTC DRUG LABEL
Date: 20120607

ACTIVE INGREDIENTS: BIOTIN 0.01 mL/100 mL
INACTIVE INGREDIENTS: WATER; ALCOHOL; BUTYLENE GLYCOL; PPG-26-BUTETH-26; POLYOXYL 40 HYDROGENATED CASTOR OIL; APIGENIN; OLEANOLIC ACID; BIOTINOYL TRIPEPTIDE-1 ; GINKGO; CALENDULA OFFICINALIS FLOWER    ; HYDROLYSED BOVINE COLLAGEN (ENZYMATIC; 2000-5000 MW); HYDROLYZED PLACENTAL PROTEIN (BOVINE); CARBOMER INTERPOLYMER TYPE A (55000 MPA.S); TROLAMINE; DMDM HYDANTOIN; METHYLCHLOROISOTHIAZOLINONE; METHYLISOTHIAZOLINONE

BIONA-VIT CONTROL Y PREVENCION CAIDA / CONTROLS AND PREVENTS HAIR LOSS

ACTIVE INGREDIENT

Biotin is a major component of the formulation acts to strengthen the hair follicle and prevents hair loss as well. It is nutrient for the hair root and helps oxygenate the hair turn slowing the loss. Provides resilience and resistence to hair.

PURPOSE

- Non invasive and painless treatment

- Keeps hair strong, rich and silky

- Nourishes the hair and scalp

KEEP OUT OF REACH OF CHILDREN

This product must be keep out reach of the children

INDICATIONS AND USAGE

This product can be applied to any person, is for topical application

WARNINGS

This product is for topical application, if this product to contact with eyes rinse immediately with water and consult your doctor.

DOSAGE AND ADMINISTRATION

- Apply amount of the hair follicle and massage until absorbed continous product. Use every 12 hours for the fast and sustained effect.

- Suitable for children, adolescents, adults and seniors.

INACTIVE INGREDIENT

This product is prepared in a non-greasy gel base, as well as biotin are other ingredients such apigenin, biotinoyl tripeptide-1 and ginkgo extract which help strengthen the hair follicle and produces a synergistic action on it.

This product do not produces adverse effects in the scalp

IMAGE OF THE LABEL